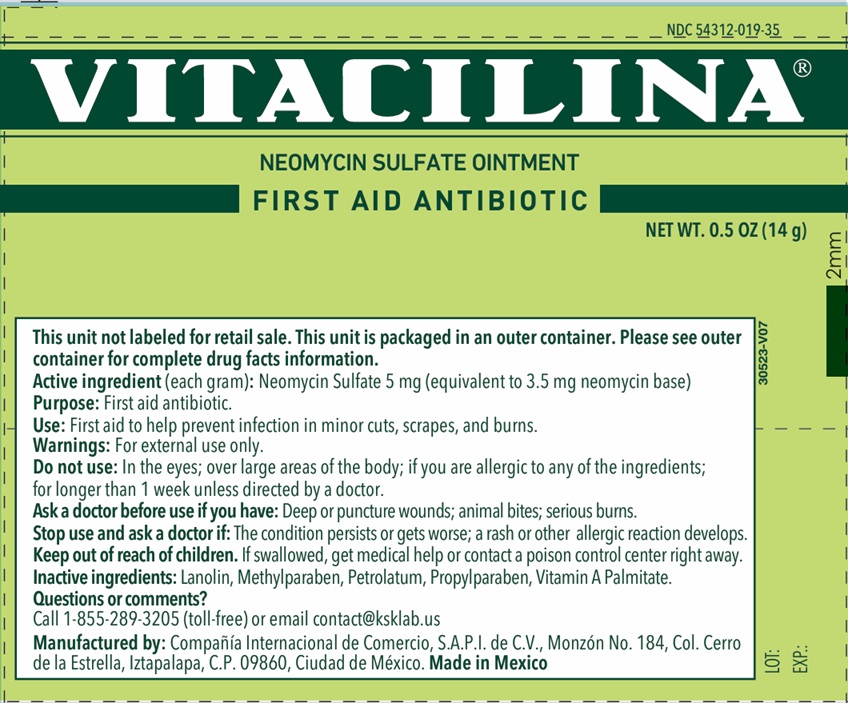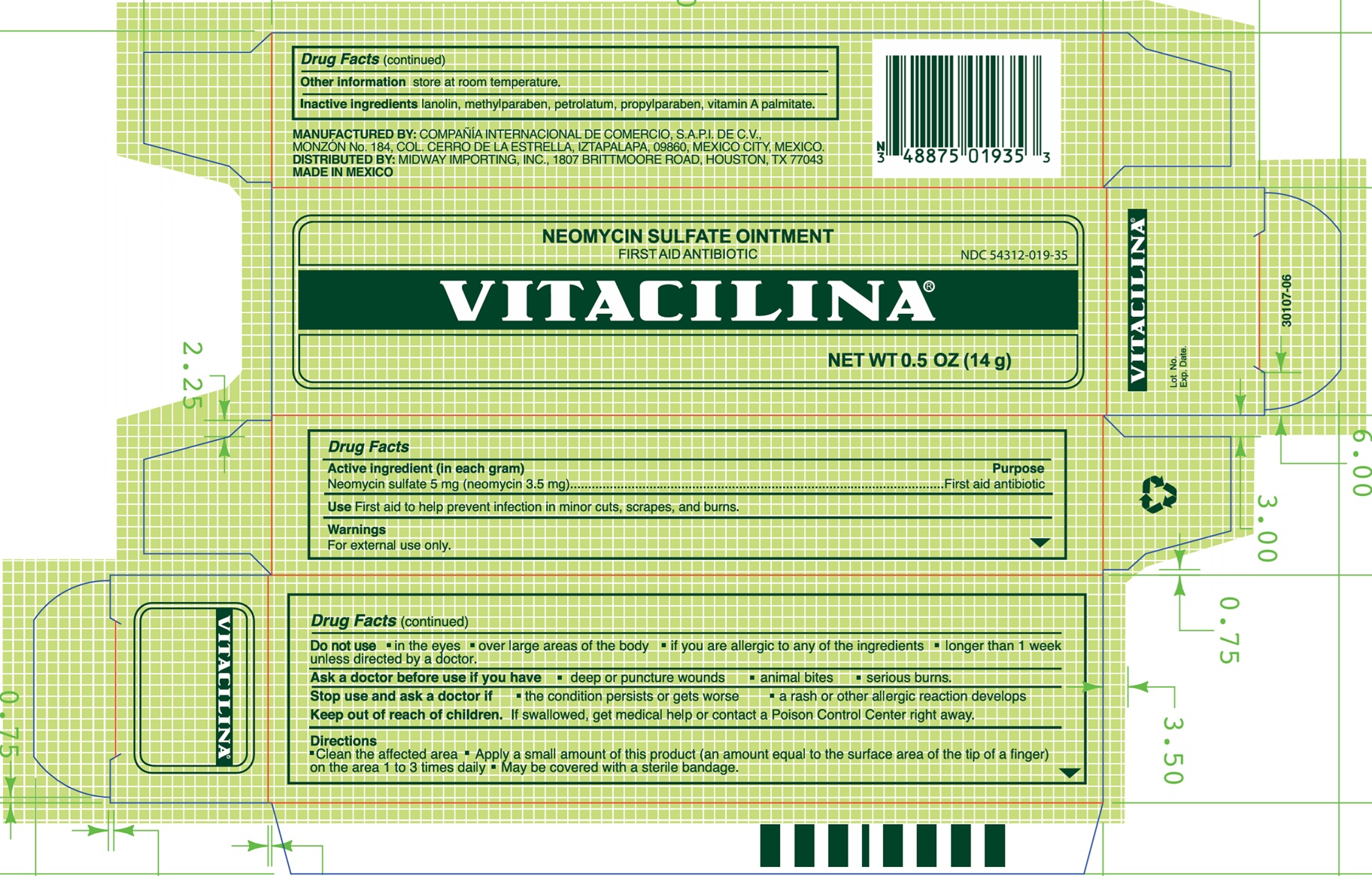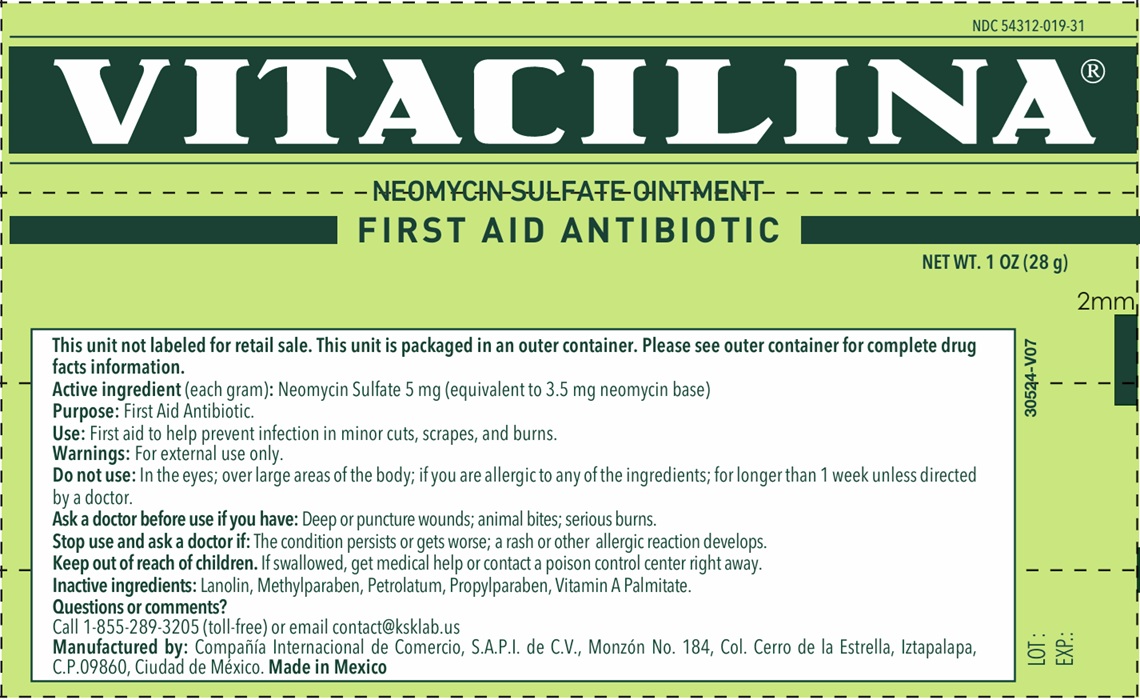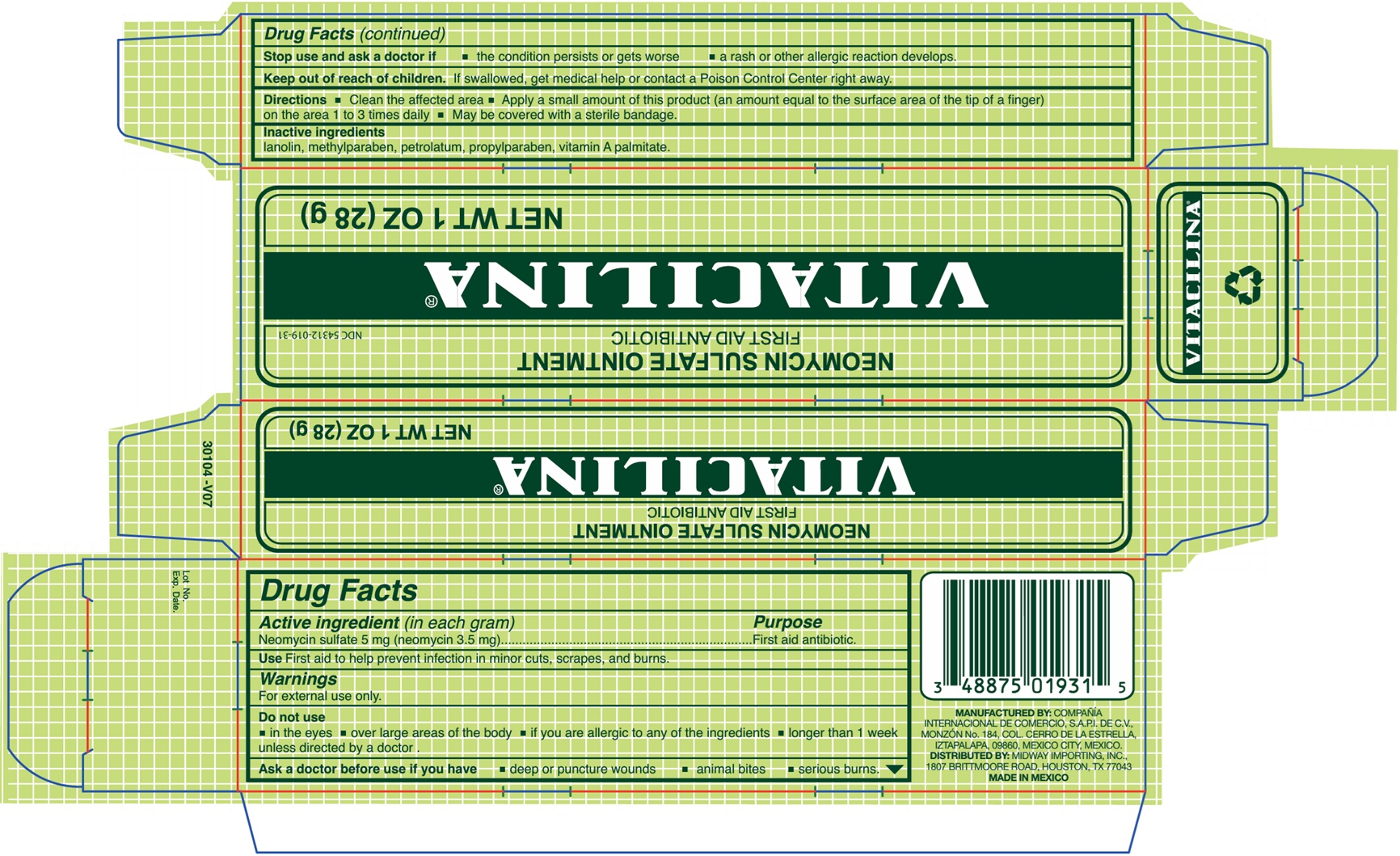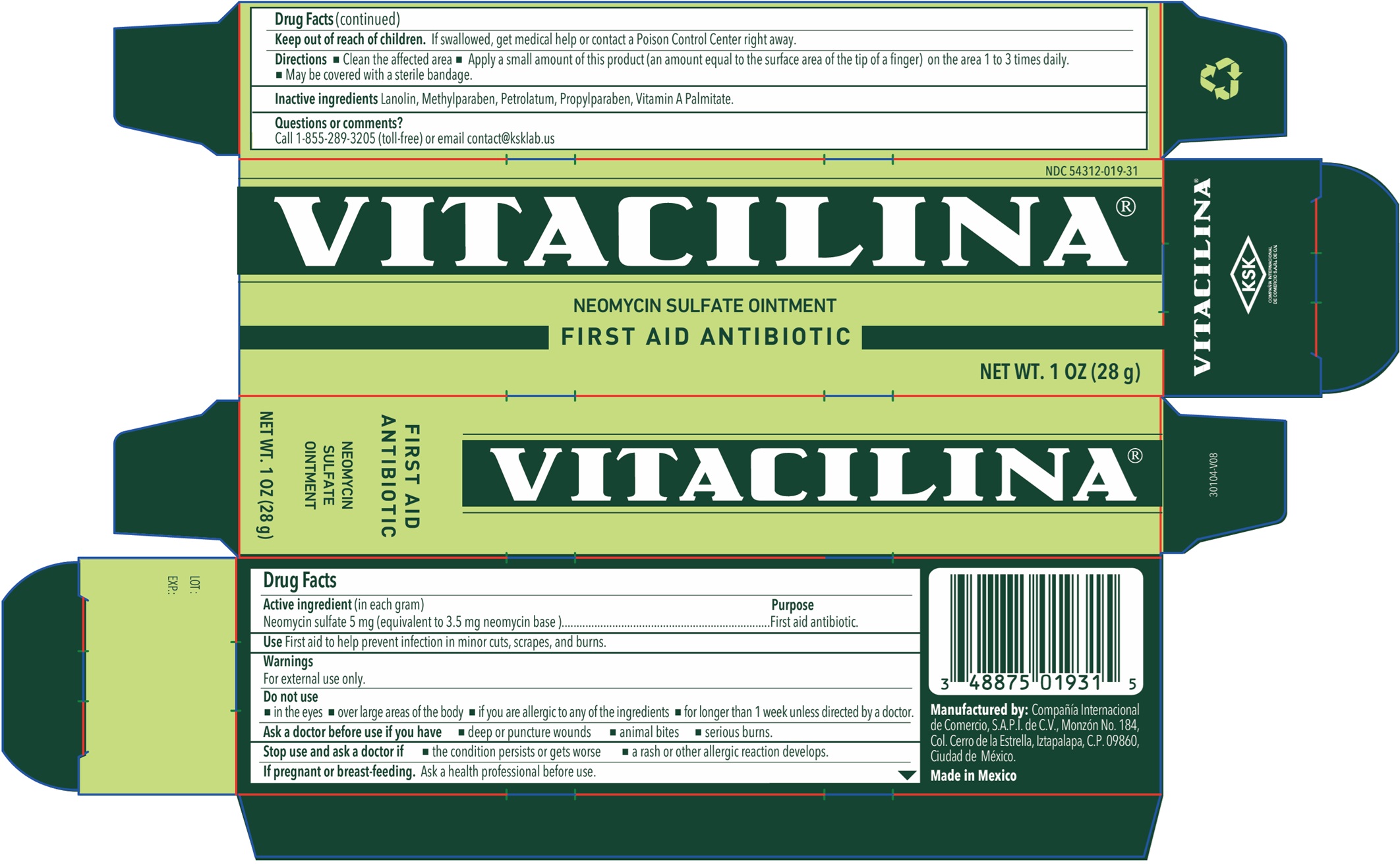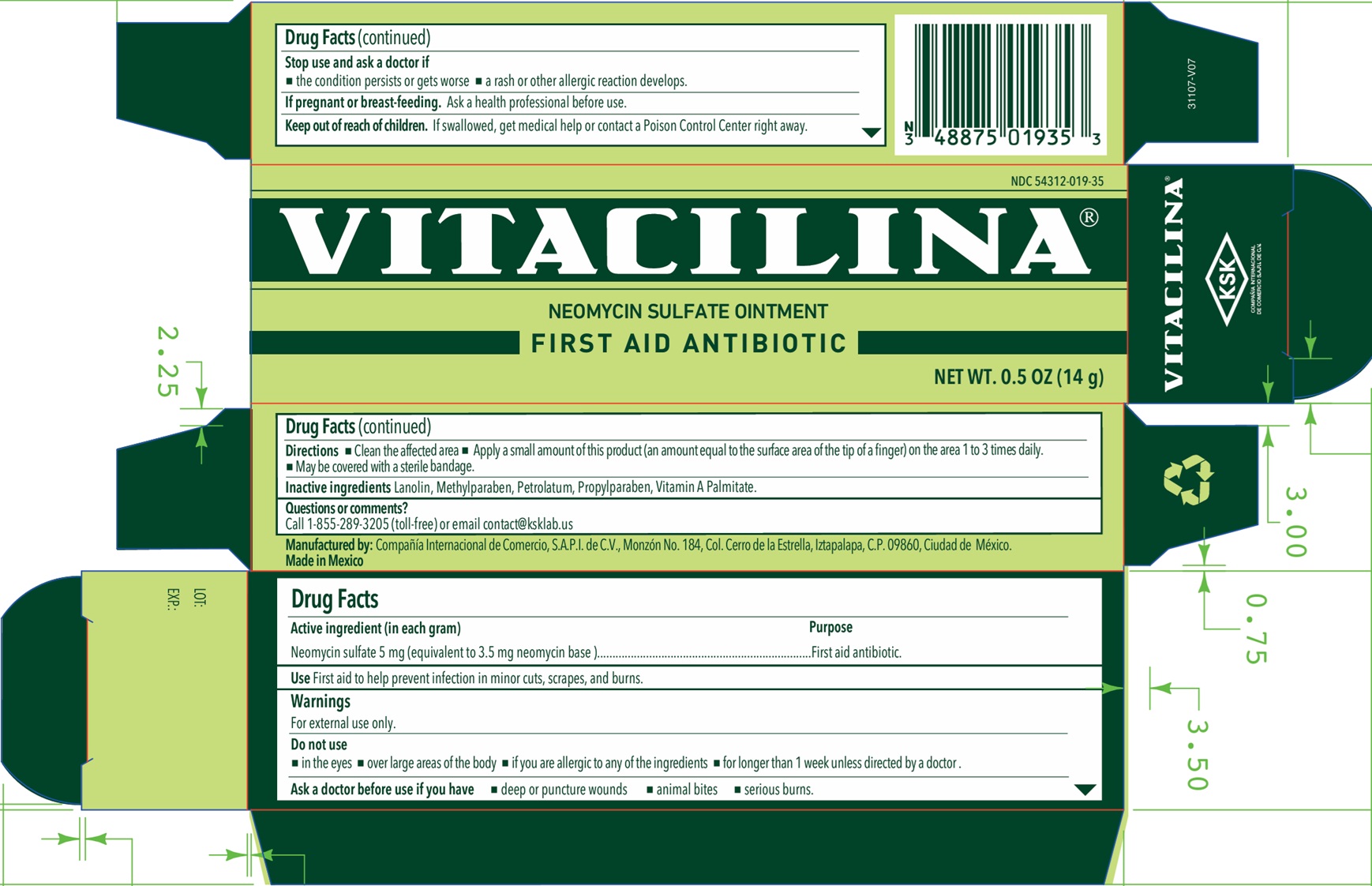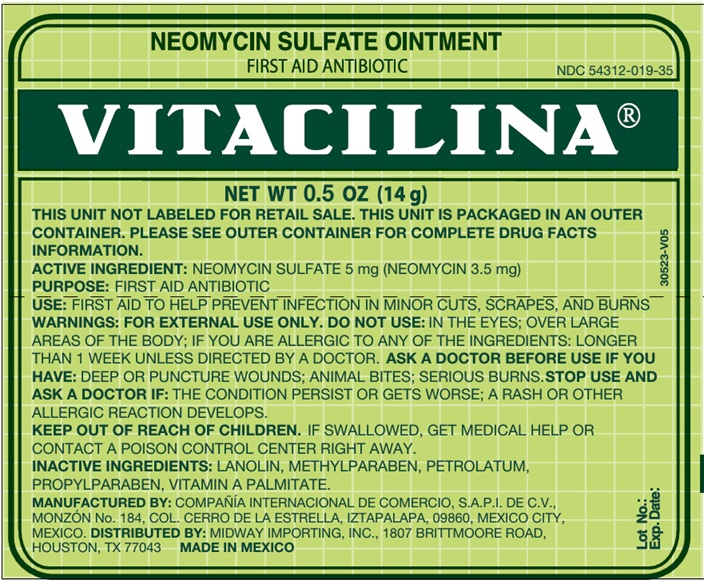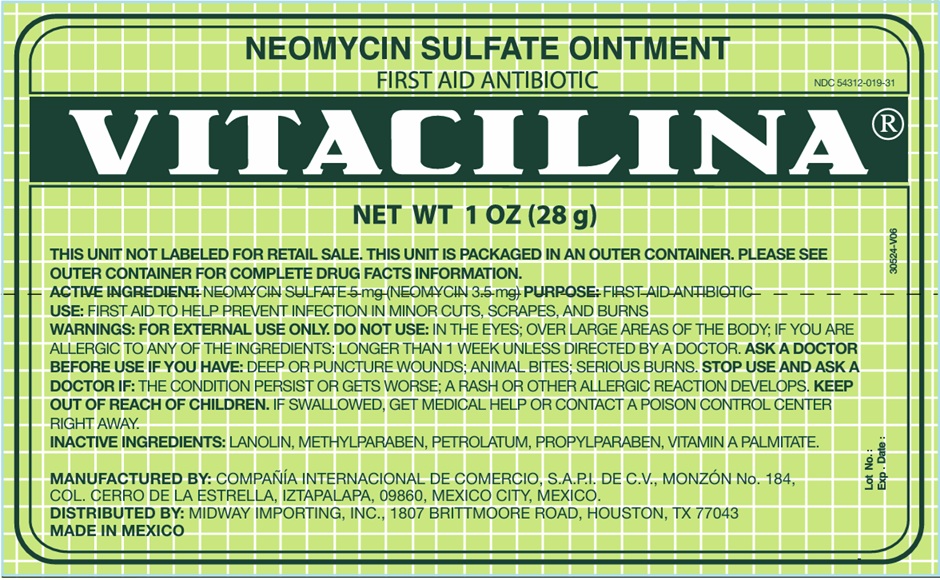 DRUG LABEL: VITACILINA NEOMYCIN SULFATE FIRST AID ANTIBIOTIC
NDC: 54312-019 | Form: OINTMENT
Manufacturer: Compania Internacional de Comercio, S.A.P.I de C.V.
Category: otc | Type: HUMAN OTC DRUG LABEL
Date: 20251119

ACTIVE INGREDIENTS: NEOMYCIN SULFATE 3.5 mg/1 g
INACTIVE INGREDIENTS: LANOLIN; METHYLPARABEN; PETROLATUM; PROPYLPARABEN; VITAMIN A PALMITATE

VITACILINA NEOMYCIN SULFATE OINTMENT FIRST AID ANTIBIOTIC

Active ingredient (in each gram)

Neomycin sulfate 5 mg (neomycin 3.5 mg)

Purpose

First aid antibiotic

Uses

First aid to help prevent infection in minor cuts, scrapes, and burns.

Warnings

For external use only

Do not use

• in the eyes • over large areas of the body • if you are allergic to any of the ingredients • longer than 1 week unless directed by a doctor

Ask a doctor before use if you have

• deep or puncture wounds • animal bites • serious burns

Stop use and ask a doctor if

• the condition persists or gets worse • a rash or other allergic reaction develops

Keep out of the reach of children.

If swallowed, get medical help or contact a Poison Control Center right away.

Directions

• Clean the affected area • Apply a small amount of this product (an amount equal to the surface area of the tip of a finger) on the area 1 to 3 times daily • May be covered with a sterile bandage

Other information

store at room temperature

Inactive ingredients

lanolin, methylparaben, petrolatum, propylparaben, vitamin A palmitate